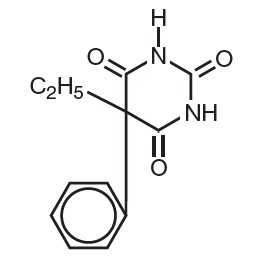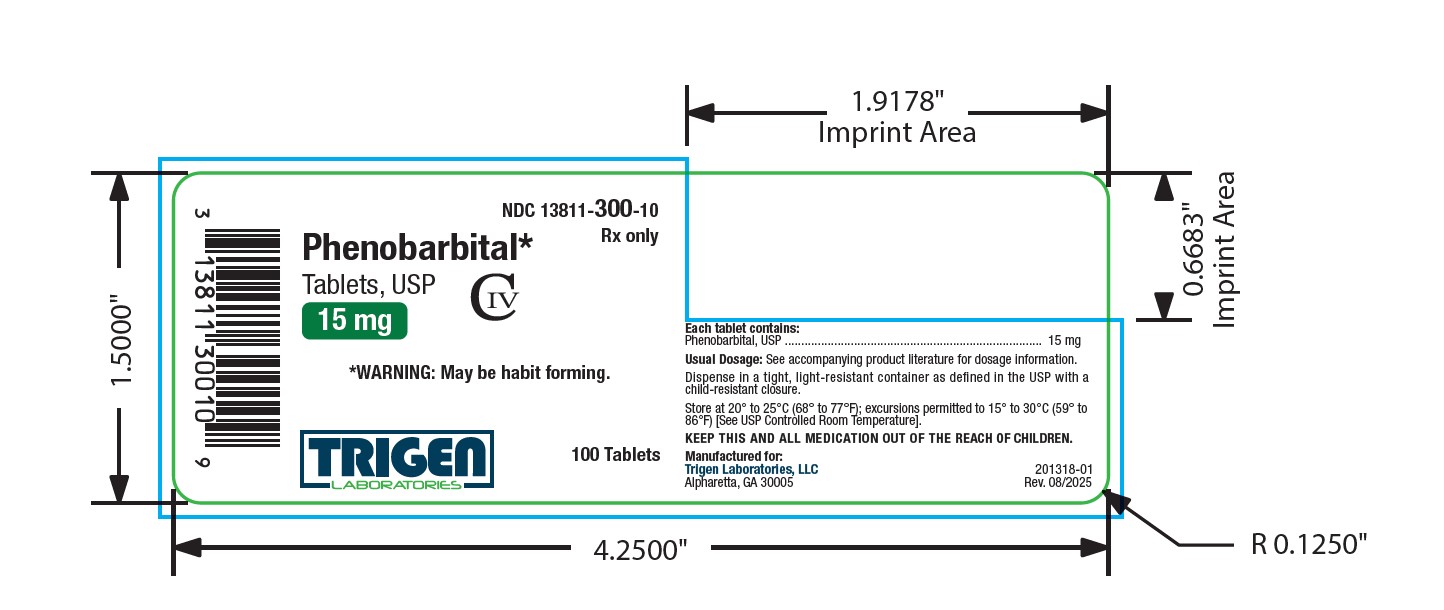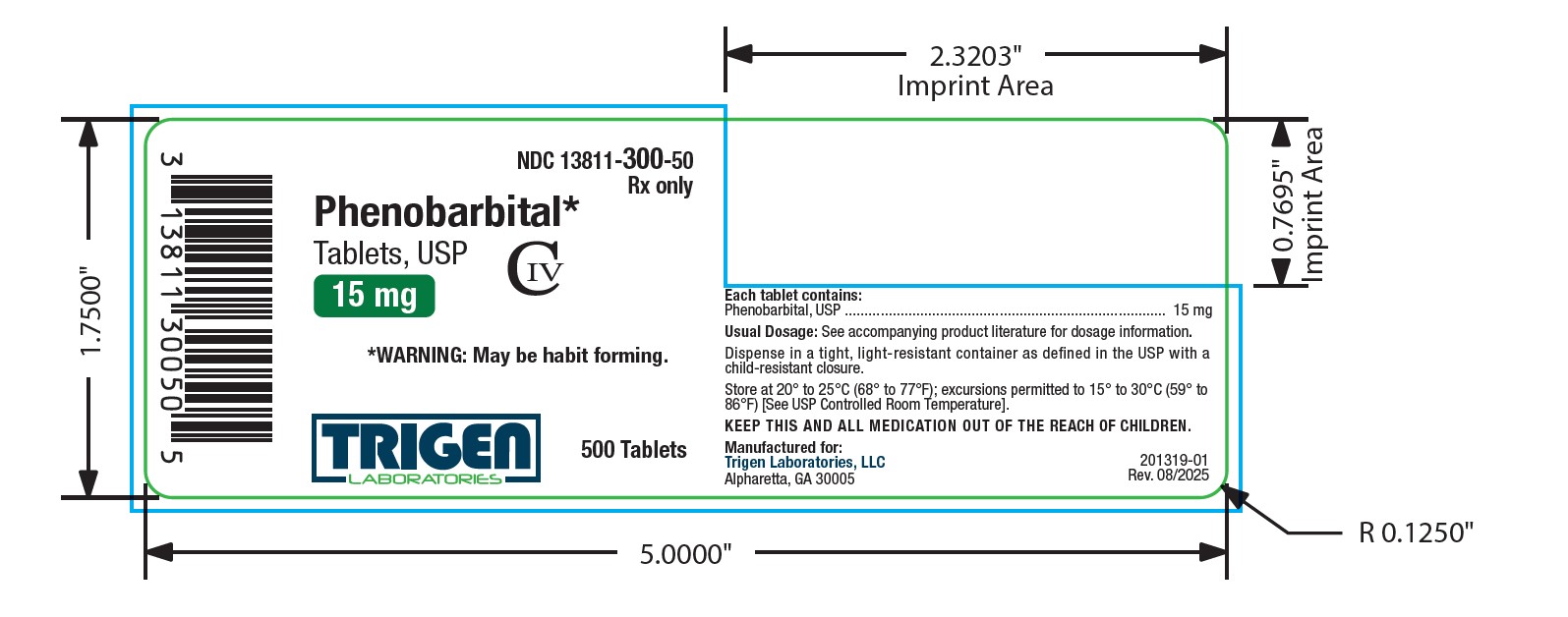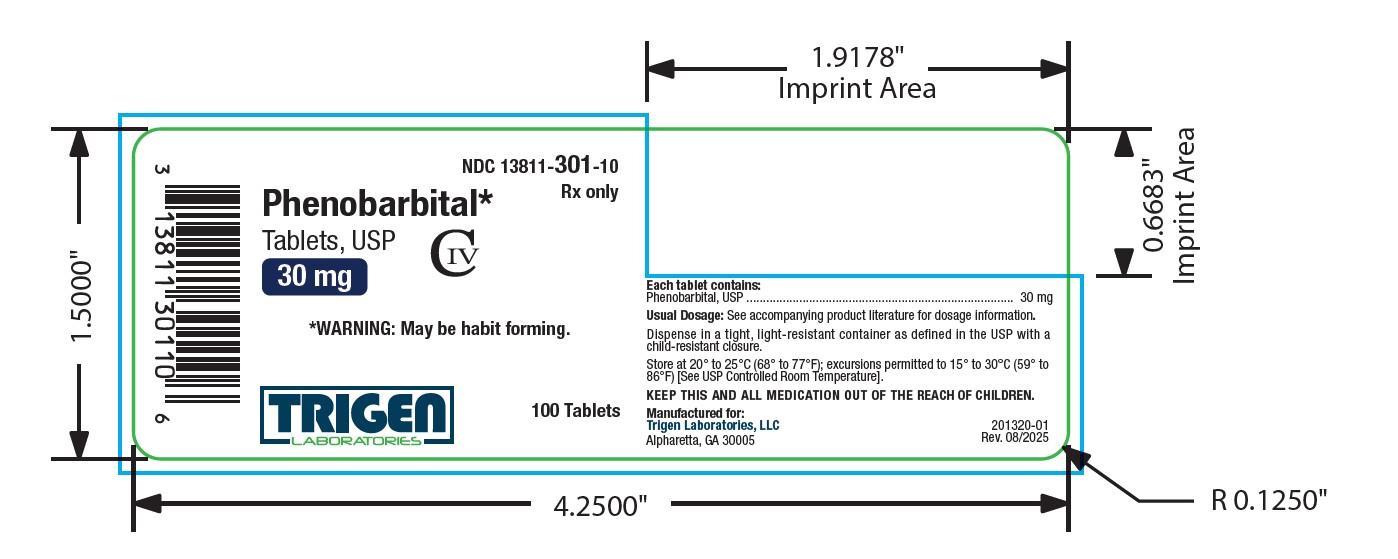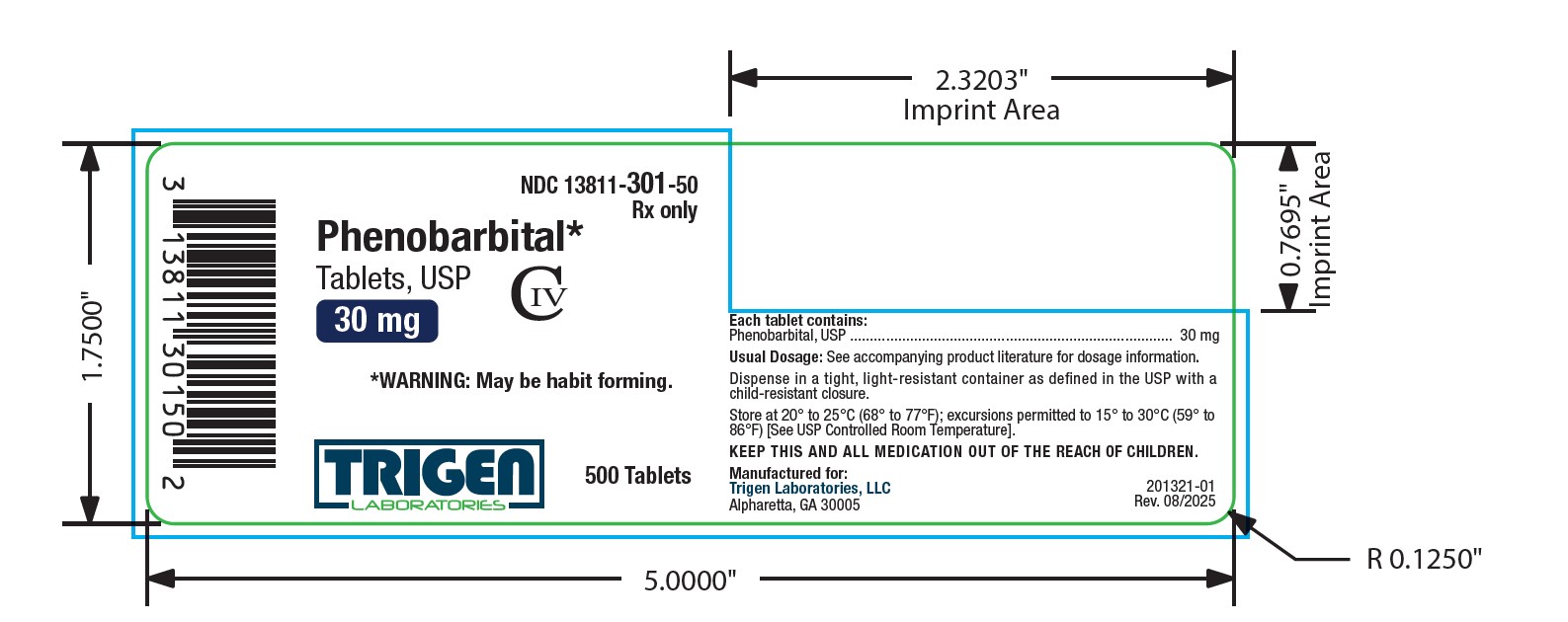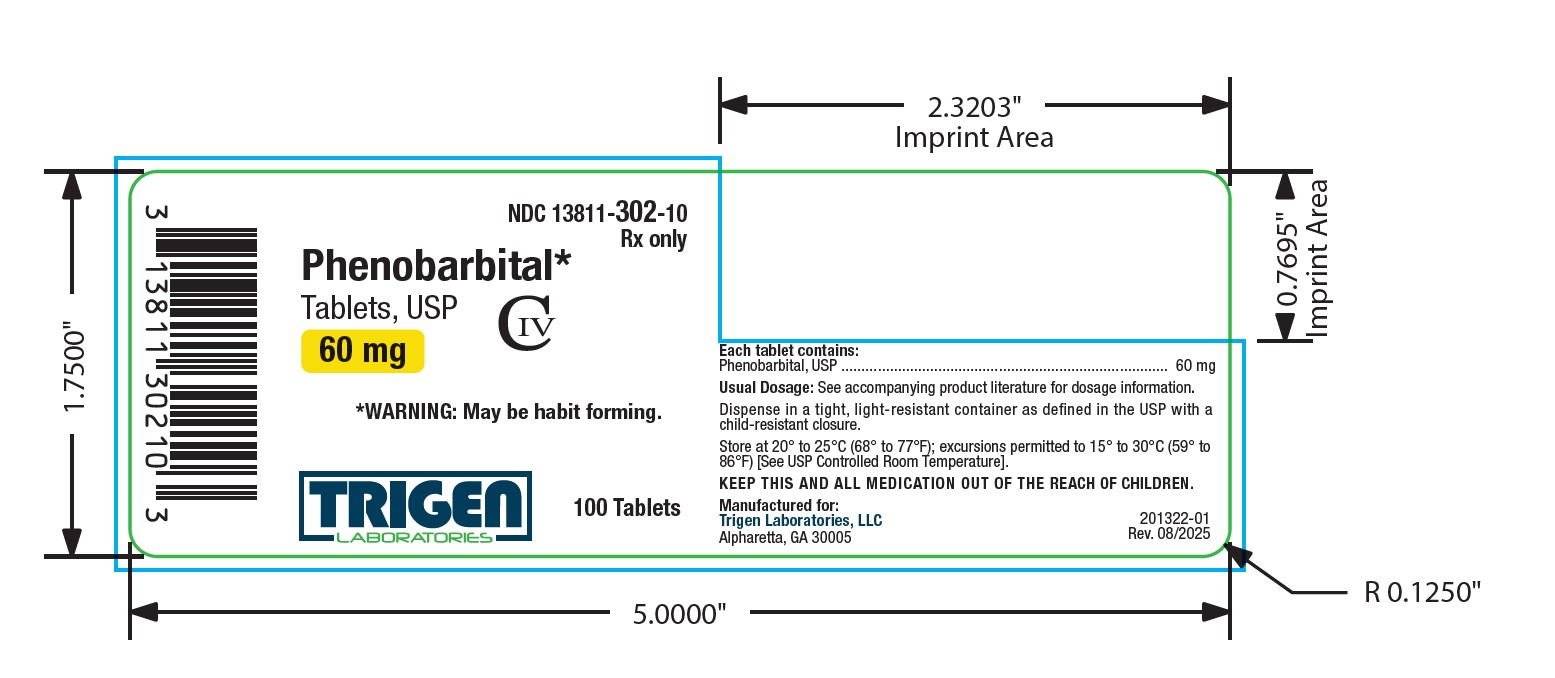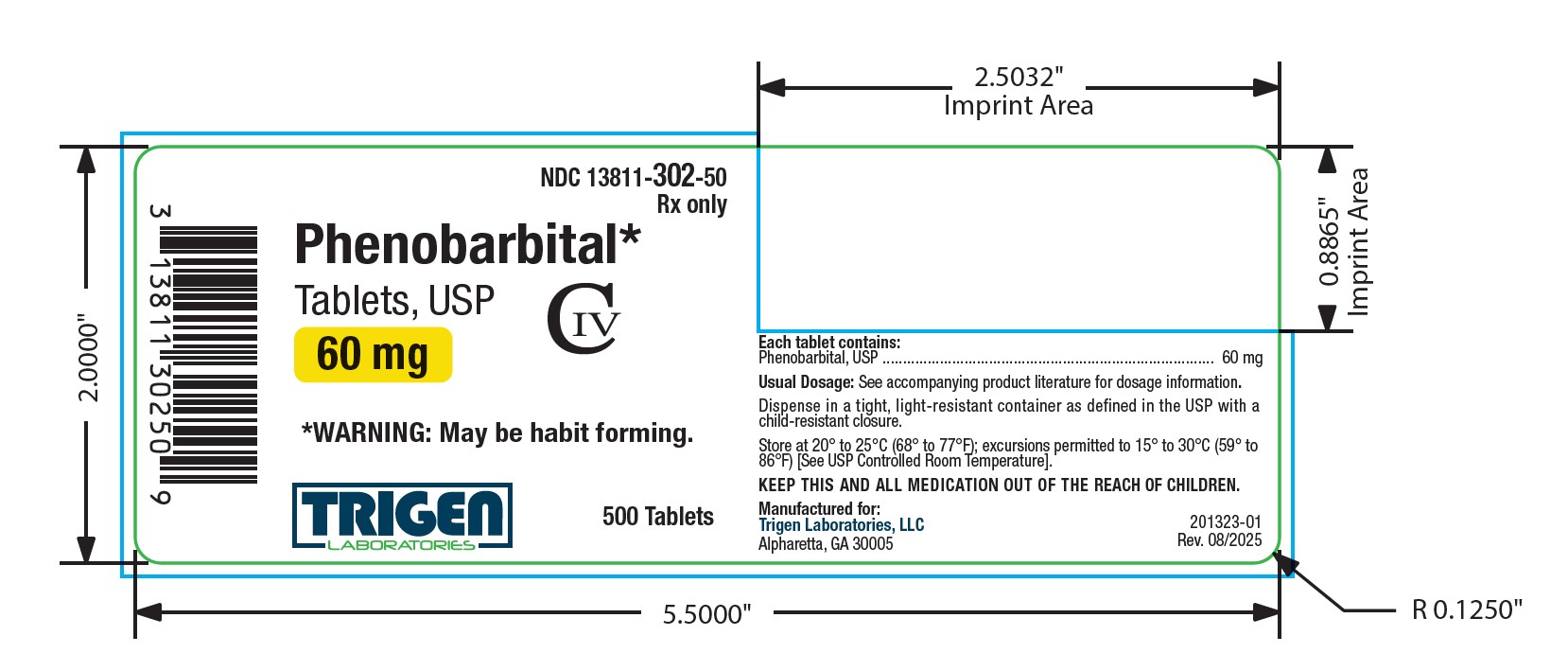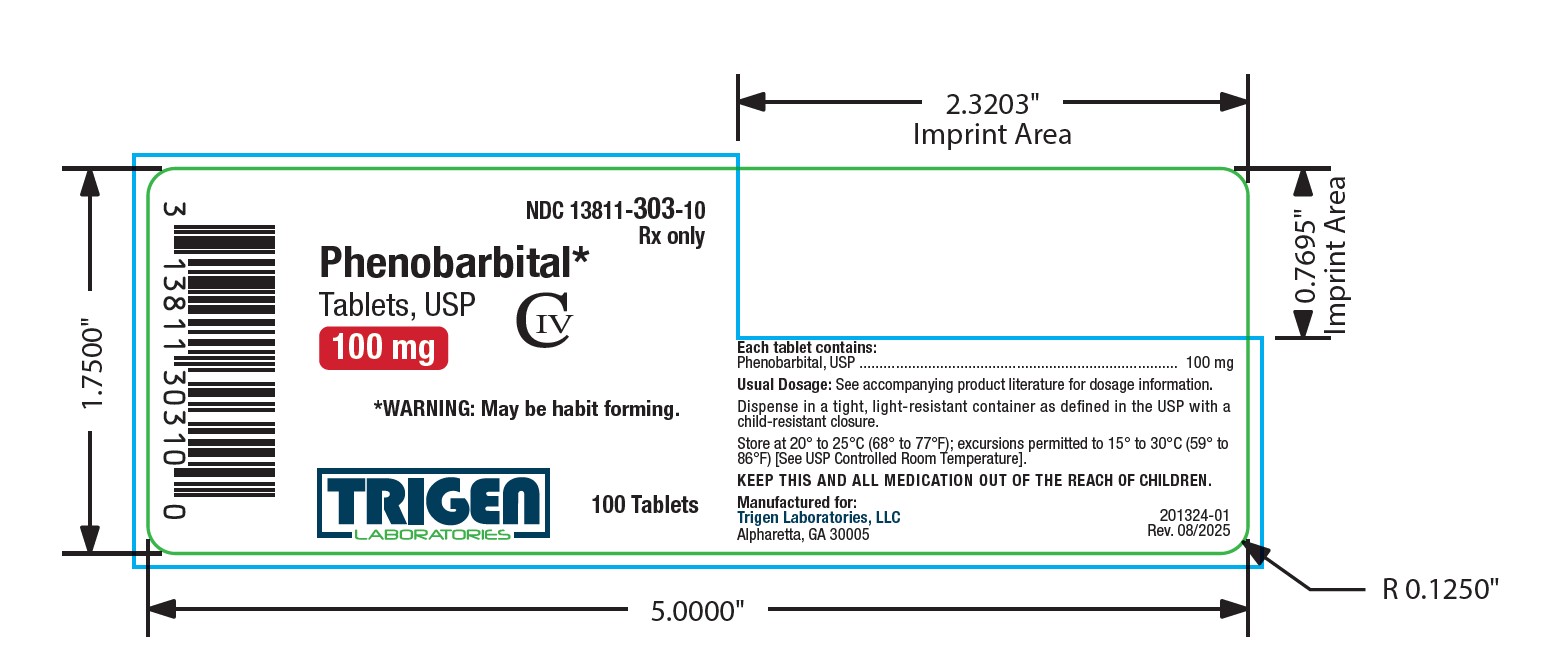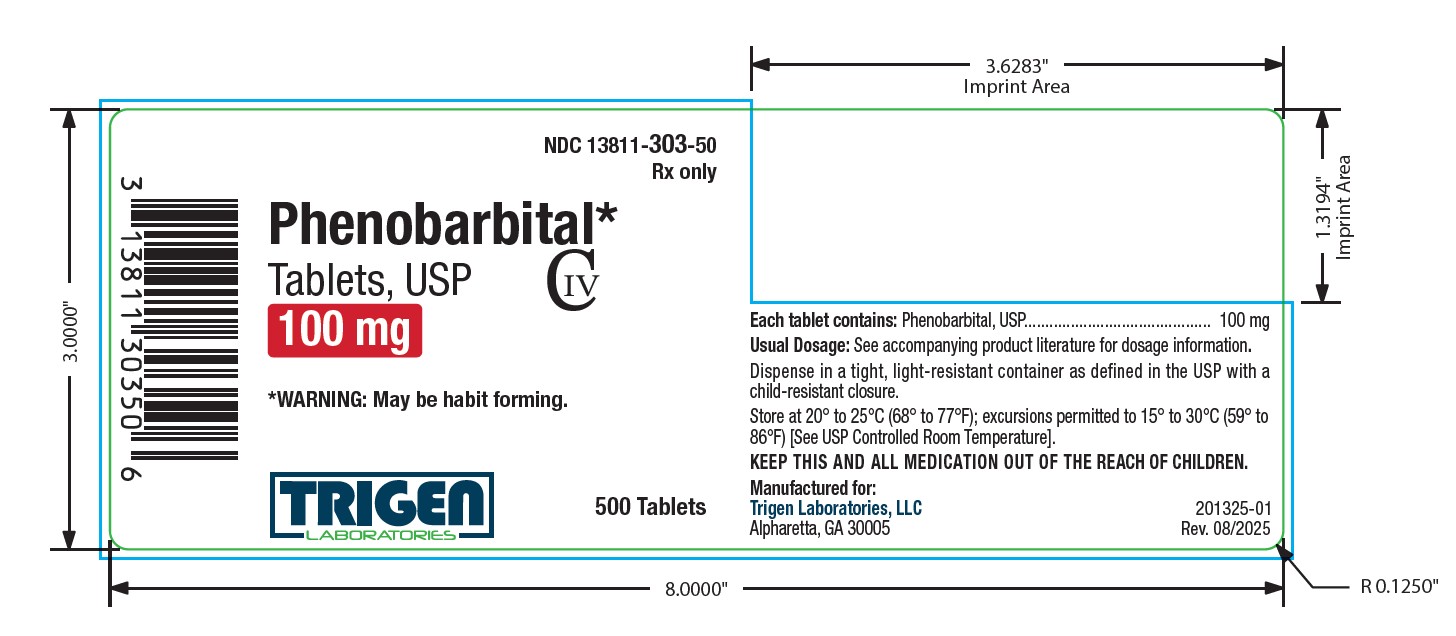 DRUG LABEL: Phenobarbital
NDC: 13811-300 | Form: TABLET
Manufacturer: Trigen Laboratories, LLC
Category: prescription | Type: HUMAN PRESCRIPTION DRUG LABEL
Date: 20250922
DEA Schedule: CIV

ACTIVE INGREDIENTS: PHENOBARBITAL 15 mg/1 1
INACTIVE INGREDIENTS: ANHYDROUS LACTOSE; CELLULOSE, MICROCRYSTALLINE; MAGNESIUM STEARATE; SILICON DIOXIDE; SODIUM STARCH GLYCOLATE TYPE A POTATO; STEARIC ACID

PHENOBARBITAL TABLETS, USP
CIV
Rx Only

DESCRIPTION

Phenobarbital is a barbituric acid derivative for oral administration and occurs as a white, odorless, slightly bitter powder that is soluble in chloroform, freely soluble in alcohol or ether, and slightly soluble in water. Its saturated solution has a pH of about 5.6. Chemically, it is 5- ethyl-5-phenylbarbituric acid with the molecular formula C12H12N2O3 (232.24). The structural formula is as follows:

Each Phenobarbital Tablet, USP contains 15 mg, 30 mg, 60 mg or 100 mg of phenobarbital, USP.

Inactive ingredients include: colloidal silicon dioxide, lactose anhydrous, magnesium stearate, microcrystalline cellulose, sodium starch glycolate, and stearic acid.

CLINICAL PHARMACOLOGY

Phenobarbital, a long-acting barbiturate, is a central nervous system depressant. In ordinary doses, the drug acts as a sedative and anticonvulsant. Its onset of action occurs within 30 minutes, and the duration of action ranges from 5 to 6 hours. It is detoxified in the liver.

INDICATIONS AND USAGE

Phenobarbital Tablets, USP are indicated for use as a sedative or anticonvulsant.

CONTRAINDICATIONS

Phenobarbital is contraindicated in patients who are hypersensitive to barbiturates. In such patients, severe hepatic damage can occur from ordinary doses and is usually associated with dermatitis and involvement of parenchymatous organs. A personal or familial history of acute intermittent porphyria represents one of the few absolute contraindications to the use of barbiturates. Phenobarbital is also contraindicated in patients with marked impairment of liver function, or respiratory disease in which dyspnea or obstruction is evident. It should not be administered to persons with known previous addiction to the sedative/hypnotic group, since ordinary doses may be ineffectual and may contribute to further addiction.

WARNINGS

In small doses, the barbiturates may increase the reaction to painful stimuli. Taken by themselves, the barbiturates cannot be relied upon to relieve pain or even to produce sedation or sleep in the presence of severe pain.

PRECAUTIONS

General Precautions:

Barbiturates induce liver microsomal enzyme activity. This accelerates the biotransformation of various drugs and is probably part of the mechanism of the tolerance encountered with barbiturates. Phenobarbital, therefore, should be used with caution in patients with decreased liver function. This drug should also be administered cautiously to patients with a history of drug dependence or abuse (see DRUG ABUSE AND DEPENDENCE).

Phenobarbital may decrease the potency of coumarin anticoagulants; therefore, patients receiving such concomitant therapy should have more frequent prothrombin determinations.
As with other sedatives and hypnotics, elderly or debilitated patients may react to barbiturates with marked excitement, depression, or confusion.

The systemic effects of exogenous hydrocortisone and endogenous hydrocortisone (cortisol) may be diminished by phenobarbital. Thus, this product should be administered with
caution to patients with borderline hypoadrenal function, regardless of whether it is of pituitary or of primary adrenal origin.

Information for Patients:

Phenobarbital may impair the mental and/or physical abilities required for the performance of potentially hazardous tasks, such as driving a car or operating machinery. The patient should be cautioned accordingly.

Drug Interactions:

Phenobarbital in combination with alcohol, tranquilizers, and other central nervous system depressants has additive depressant effects, and the patient should be so advised. Patients taking this drug should be warned not to exceed the dosage recommended by their physician. Toxic effects and fatalities have occurred following overdoses of phenobarbital alone and in combination with other central nervous system depressants. Caution should be exercised in prescribing unnecessarily large amounts of
phenobarbital for patients who have a history of emotional disturbances or suicidal ideation or who have misused alcohol and other CNS drugs(see OVERDOSAGE).

Usage in Pregnancy:

Pregnancy Category B - Reproduction studies have been performed in animals and have revealed no evidence of impaired fertility or harm to the fetus due to phenobarbital. There are, however, no adequate and well-controlled studies in pregnant women. Because animal reproduction studies are not always predictive of human response, this drug should be used during pregnancy only if clearly needed.

Nursing Mothers:

Caution should be exercised when phenobarbital is administered to a nursing woman.

ADVERSE REACTIONS

The following adverse reactions have been reported:

CNS Depression:

Residual sedation or “hangover”, drowsiness, lethargy, and vertigo. Emotional disturbances and phobias may be accentuated. In some persons, barbiturates such as phenobarbital repeatedly produce excitement rather than depression, and the patient may appear to be inebriated. Like other non-analgesic hypnotic drugs, barbiturates, such as phenobarbital, when given in the presence of pain, may cause restlessness, excitement, and even delirium. Rarely, the use of barbiturates results in localized or diffused myalgic, neuralgic, or arthritic pain, especially in psychoneurotic patients with insomnia. The pain may appear in paroxysms, is most intense in the early morning hours, and is most frequently located in the region of the neck, shoulder girdle, and upper limbs. Symptoms may last for days after the drug is discontinued.

Respiratory/Circulatory:

Respiratory depression, apnea, circulatory collapse.

Allergic:

Acquired hypersensitivity to barbiturates consists chiefly in allergic reactions that occur especially in persons who tend to have asthma, urticaria, angioedema, and similar conditions. Hypersensitivity reactions in this category include localized swelling, particularly of the eyelids, cheeks, or lips, and erythematous dermatitis. Rarely, exfoliative dermatitis (e.g., Stevens-Johnson syndrome and toxic epidermal necrolysis) may be caused by phenobarbital and can prove fatal. The skin eruption may be associated with fever, delirium, and marked degenerative changes in the liver and other parenchymatous organs. In a few cases, megaloblastic anemia has been associated with the chronic use of phenobarbital.

Other:

Nausea and vomiting; headache.

To report SUSPECTED ADVERSE REACTIONS, contact Trigen Laboratories, LLC at 1-800-541-4802, or FDA at 1-800-FDA-1088 or www.fda.gov/medwatch.

DRUG ABUSE AND DEPENDENCE

Controlled Substance - Phenobarbital is a Schedule IV drug.

Dependence:

Prolonged, uninterrupted use of barbiturates (particularly the short-acting drugs), even in therapeutic doses, may result in psychic and physical dependence. Withdrawal symptoms due to physical dependence following chronic use of large doses of barbiturates may include delirium, convulsions, and death.

OVERDOSAGE

The signs and symptoms of barbiturate poisoning are referable especially to the central nervous system and the cardiovascular system. Moderate intoxication resembles alcoholic inebriation. In severe intoxication, the patient is comatose, the level of reflex activity conforming in a general way to the intensity of the central depression. The deep reflexes may persist for some time despite coexistent coma. The Babinski sign is often positive. The EEG may be of the “burst- suppression” type, with brief periods of electrical silence. The pupils may be constricted and react to light, but late in the course of barbiturate poisoning they may show hypoxic paralytic dilatation. Respiration is affected early. Breathing may be either slow or rapid and shallow; Cheyne-Stokes rhythm may be present. Respiratory minute volume is diminished, and hypoxia and respiratory acidosis may develop. The blood pressure falls, owing partly to depression of medullary vasomotor centers; partly to a direct action of the drug on the myocardium, sympathetic ganglia, and vascular smooth muscle; partly to hypoxia.

The patient thus develops a typical shock syndrome, with a weak and rapid pulse, cold and clammy skin, and a rise in the hematocrit. Respiratory complications (atelectasis, pulmonary edema, and bronchopneumonia) and renal failure are much dreaded and not infrequent concomitant of severe barbiturate poisoning. There is usually hypothermia, sometimes with temperatures as low as 32°C.

Treatment:

General management should consist of symptomatic and supportive therapy, including gastric lavage, administration of intravenous fluids, and maintenance of blood pressure, body
temperature and adequate respiratory exchange. Dialysis will increase the rate of removal of barbiturates from the body fluids. Antibiotics may be required to control pulmonary complications.

DOSAGE AND ADMINISTRATION

Oral Sedative Dose, Adults - 30 to 120 mg daily in 2 or 3 divided doses. Children - 6 mg/kg of body weight daily in 3 divided doses.

Oral Hypnotic Dose, Adults - 100 to 320 mg.

Oral Anticonvulsant Dose, Adults - 50 to 100 mg 2 or 3 times daily.

Children - 15 to 50 mg 2 or 3 times daily.

HOW SUPPLIED

Phenobarbital Tablets, USP 15 mg: White, round, tablets debossed “315" on one side. The opposite side is plain.

Available in bottles of 100 tablets, NDC 13811-300-10 and 500 tablets, NDC 13811-300-50.

Phenobarbital Tablets, USP 30 mg: White, round, tablets scored on one side. The scored side is debossed “330" above the score. The opposite side is plain.

Available in bottles of 100 tablets, NDC 13811-301-10 and 500 tablets, NDC 13811-301-50.

Phenobarbital Tablets, USP 60 mg: White, round, tablets scored on one side. The scored side is debossed “360" above the score. The opposite side is plain.

Available in bottles of 100 tablets, NDC 13811-302-10 and 500 tablets, NDC 13811-302-50.

Phenobarbital Tablets, USP 100 mg: White, round, tablets scored on one side. The scored side is debossed “310" above the score. The opposite side is plain.

Available in bottles of 100 tablets, NDC 13811-303-10 and 500 tablets, NDC 13811-303-50.

Store at 20° to 25°C (68° to 77°F) [See USP Controlled Room Temperature]. Protect from light and moisture. Dispense in a tight, light-resistant container as defined in the USP using a child-resistant closure.

Manufactured for:
Trigen Laboratories, LLC
Alpharetta, GA, 30005

201335-01 Rev. 08/2025

PRINCIPAL DISPLAY PANEL

Phenobarbital Tablets, USP 15 mg

100ct bottle label

PRINCIPAL DISPLAY PANEL

Phenobarbital Tablets, USP 15 mg

500ct Bottle Label

PRINCIPLE DISPLAY PANEL

Phenobarbital Tablets, USP 30 mg

100ct Bottle Label

PRINCIPLE DISPLAY PANEL

Phenobarbital Tablets, USP 30 mg

500ct Bottle Label

PRINCIPLE DISPLAY PANEL

Phenobarbital Tablets, USP 60 mg

100ct Bottle Label

PRINCIPLE DISPLAY PANEL

Phenobarbital Tablets, USP 60 mg

500ct Bottle Label

PRINCIPLE DISPLAY PANEL

Phenobarbital Tablets, USP 100 mg

100ct Bottle Label

PRINCIPLE DISPLAY PANEL

Phenobarbital Tablets, USP 100 mg

500ct Bottle Label